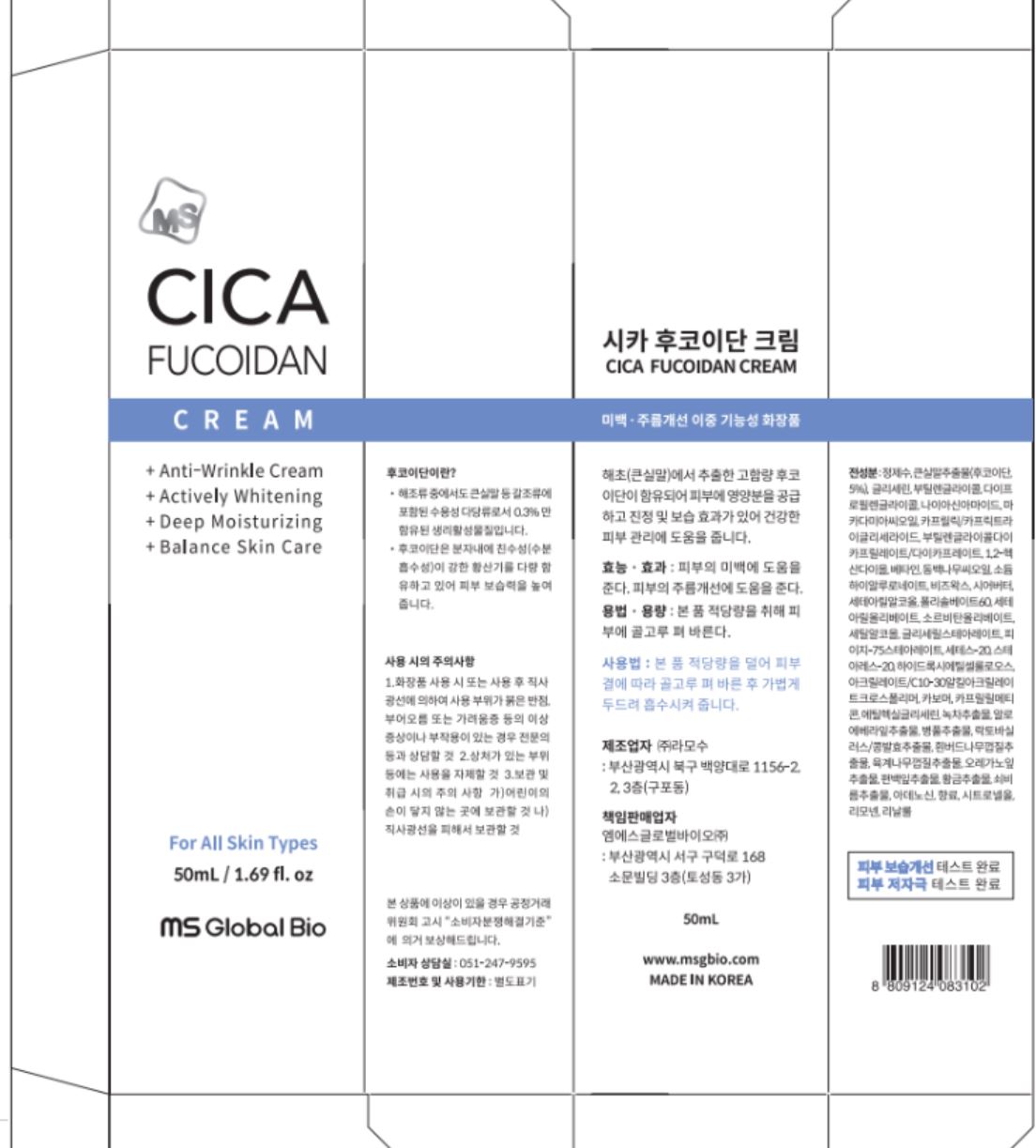 DRUG LABEL: CICA FUCOIDAN
NDC: 79630-0002 | Form: CREAM
Manufacturer: MS Global Bio Co., Ltd.
Category: otc | Type: HUMAN OTC DRUG LABEL
Date: 20200914

ACTIVE INGREDIENTS: NIACINAMIDE 2 g/100 mL; WATER 3 g/100 mL
INACTIVE INGREDIENTS: GLYCERIN; ADENOSINE; BUTYLENE GLYCOL

Drug Facts

ACTIVE INGREDIENT

niacinamide

PURPOSE

anti-wrinkle, whitening

KEEP OUT OF REACH OF THE CHILDREN

WARNINGS

■ For external use only.Keep out of reach of children. If swallowed, get medical help or contacta Poison Control Center right away. Avoid contact with eyes. Discontinue use if signs of irritation appear

DOSAGE AND ADMINISTRATION

for external use only

INACTIVE INGREDIENT

Water, Cladosiphon Extract(Fucoidan), Glycerin, Butylene Glycol, Dipropylene Glycol, Niacinamide, Macadamia Ternifolia Seed Oil, Caprylic/Capric Triglyceride, Butylene Glycol, Dicaprylate/Dicaprate, 1,2-Hexanediol, Betaine, Camellia Japonica Seed Oil, Sodium Hyaluronate, Beeswax, Butyrospermum Parkii (Shea) Butter, Cetearyl Alcohol, olysorbate 60, Cetearyl Olivate, Sorbitan Olivate, Cetyl Alcohol, Glyceryl Stearate, PEG-75 Stearate, Ceteth-20, Steareth-20, Hydroxyethylcellulose, Acrylates/C10-30 Alkyl Acrylate Crosspolymer, Carbomer, Caprylyl Methicone, Ethylhexylglycerin, Camellia Sinensis Leaf Extract, Aloe Barbadensis Leaf Extract, Centella Asiatica Extract, Lactobacillus/Soybean Ferment Extract, Salix Alba (Willow) Bark Extract, Cinnamomum Cassia Bark Extract, Origanum Vulgare Leaf Extract, Chamaecyparis Obtusa Leaf Extract, Scutellaria Baicalensis Root Extract, Portulaca Oleracea Extract, Adenosine, Flavor, Citronellol, Limonene, Linalool

INDICATIONS AND USAGE

■After water lotion application, dispense an ample amount into your palm. Smooth on the face in gentle rolling motions.